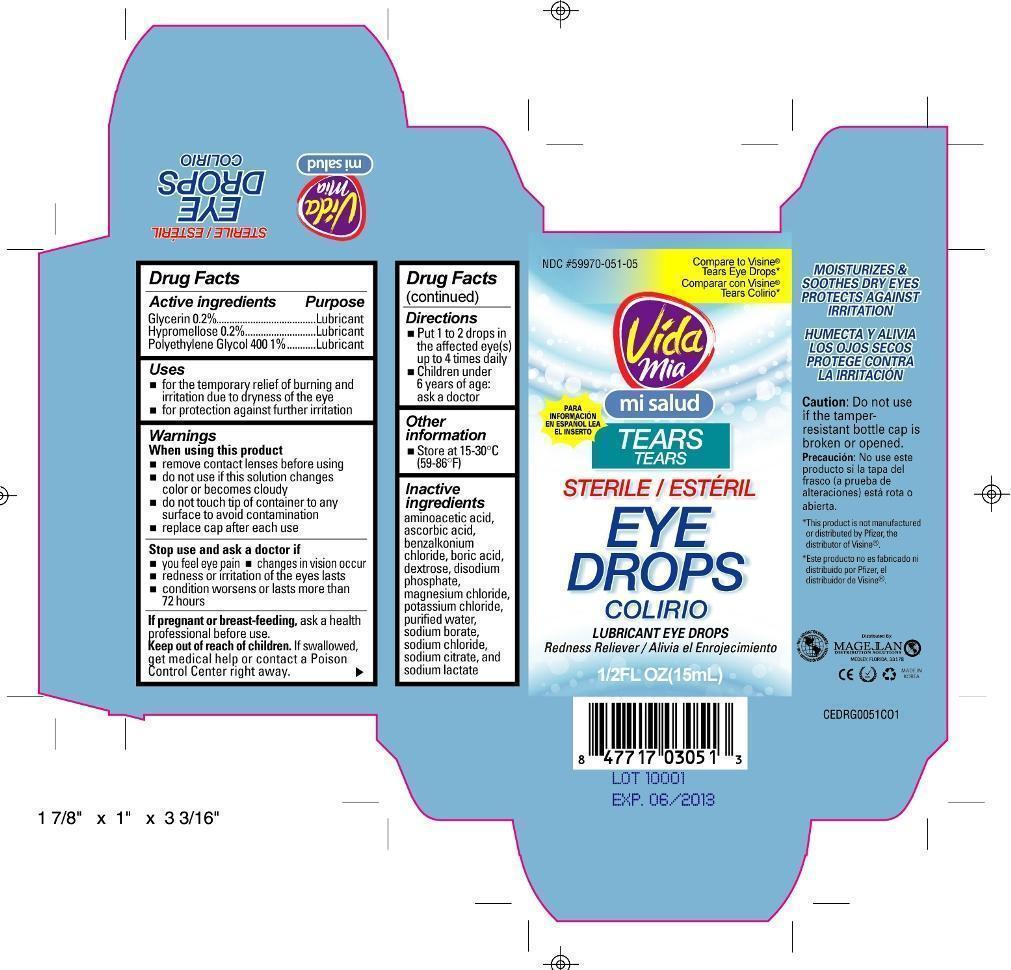 DRUG LABEL: Tears lubricant 
NDC: 59970-051 | Form: LIQUID
Manufacturer: Navarro Discount Pharmacies,LLC
Category: otc | Type: HUMAN OTC DRUG LABEL
Date: 20120816

ACTIVE INGREDIENTS: GLYCERIN 2 mg/1 mL; HYPROMELLOSES 2 mg/1 mL; POLYETHYLENE GLYCOL 400 10 mg/1 mL
INACTIVE INGREDIENTS: GLYCINE; ASCORBIC ACID; BENZALKONIUM CHLORIDE; BORIC ACID; DEXTROSE; MAGNESIUM CHLORIDE; POTASSIUM CHLORIDE; WATER; SODIUM BORATE; SODIUM CHLORIDE; SODIUM CITRATE; SODIUM LACTATE

Drug Facts

Active Ingredient

Glycerin 0.2%

Hypromellose 0.2%

Polyethylene Glycol 400 1%

Purpose

Lubricant

Lubricant

Lubricant

Use

- for the temporary relief of burning and irritation due to dryness of the eye
- for protection against further irritation

Warnings

When using this product

- remove contact lenses before using
- do not use if this solution changes color or become cloudy
- do not touch tip of container to any surface to avoid contamination
- replace cap after each use

Stop use and ask a doctor if

- you feel eye pain
- changes in vision occur
- redness or irritation of the eye lasts
- condition worsens or lasts more than 72 hours

If pregnant or breast-feeding,

ask a health professional before use.

Keep out of reach of children.

If swallowed, get medical help or contact a Poison Control Center right away.

Directions

- Put 1 to 2 drops in the affected eye(s) up to 4 times daily
- children under 6 years of age: ask a doctor

Other information

- store between 15° to 30°C (59°F to 86°F)

Inactive ingredients

aminoacetic acid, ascorbic acid, benzalkonium chloride, boric acid, dextrose, disodium phosphate, magnesium chloride, potassium chloride, purified water, sodium borate, sodium chloride, sodium citrate, sodium lactate

Package principal display panel

Tears eye drop